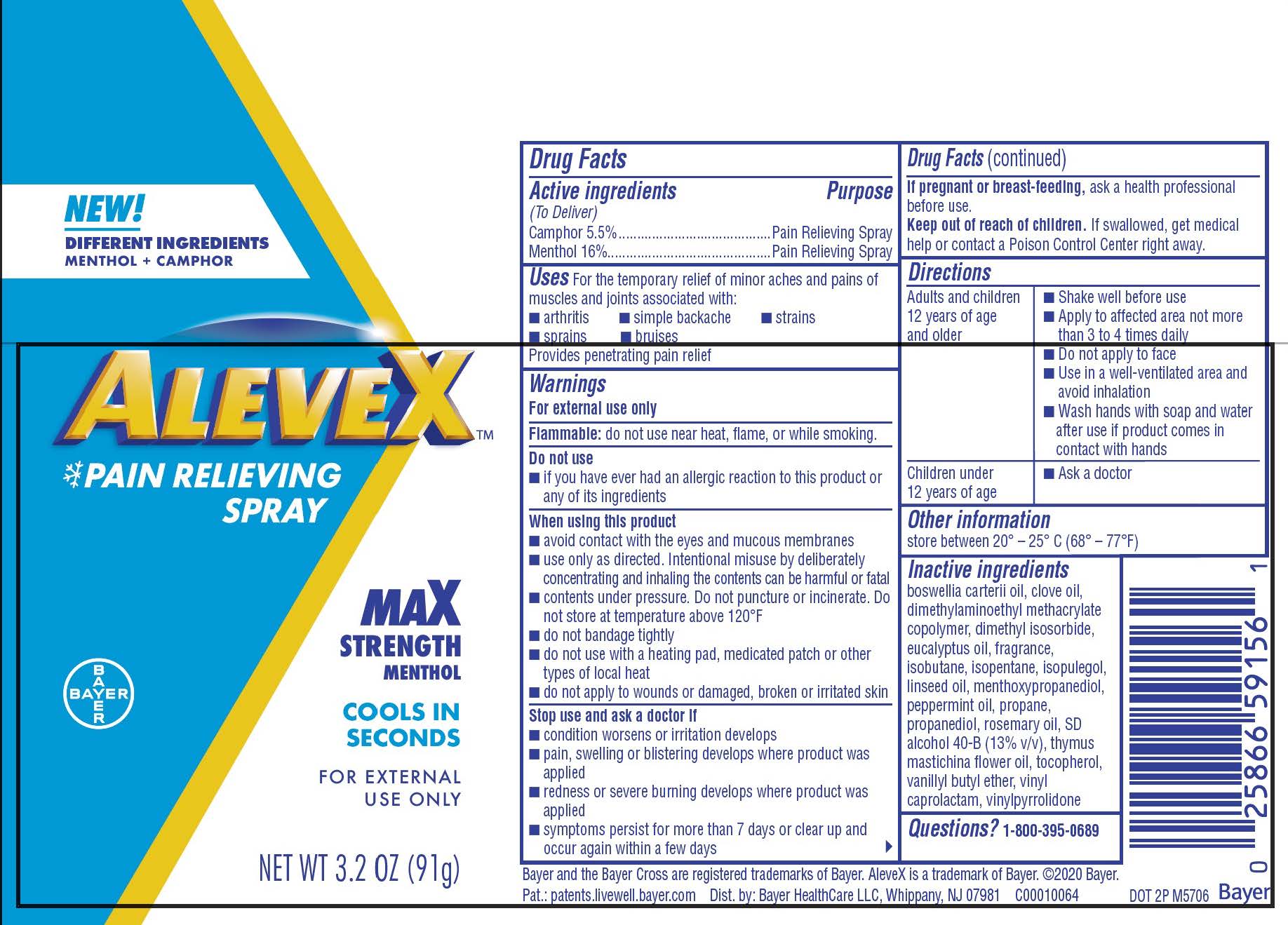 DRUG LABEL: AleveX
NDC: 0280-0049 | Form: SPRAY
Manufacturer: Bayer HealthCare LLC
Category: otc | Type: HUMAN OTC DRUG LABEL
Date: 20251204

ACTIVE INGREDIENTS: CAMPHOR (SYNTHETIC) 5.5 mg/1 g; MENTHOL 16 mg/1 g
INACTIVE INGREDIENTS: CARBOMER INTERPOLYMER TYPE A (ALLYL SUCROSE CROSSLINKED); ISOBUTANE; PEPPERMINT OIL; ALCOHOL; PROPANEDIOL; ROSEMARY OIL; PROPANE; FRANKINCENSE OIL; DIMETHYLAMINOETHYL METHACRYLATE - BUTYL METHACRYLATE - METHYL METHACRYLATE COPOLYMER; LINSEED OIL; TOCOPHEROL; 3-((L-MENTHYL)OXY)PROPANE-1,2-DIOL; ISOPENTANE; VANILLYL BUTYL ETHER; N-VINYLCAPROLACTAM; THYMUS MASTICHINA FLOWERING TOP OIL; ISOPULEGOL; N-VINYLPYRROLIDINONE; CLOVE OIL; DIMETHYL ISOSORBIDE; EUCALYPTUS OIL

Aleve X Dry Spray UI1614336

Drug Facts

Active ingredients

(To Deliver)

Camphor 5.5%

Menthol 16%

Purpose

Pain Relieving Spray

INDICATIONS AND USAGE

For the temporary relief of minor aches and pains of muscles and joints associated with:

- arthritis
- simple backache
- strains
- sprains
- bruises

Provides penetrating pain relief

Warnings

For external use only

Flammable: do not use near heat, flame, or while smoking.

Do not use

- if you have ever had an allergic reaction to this product or any of its ingredients

When using this product

- avoid contact with the eyes and mucous membranes
- use only as directed. Intentional misuse by deliberately concentrating and inhaling the contents can be harmful or fatal
- contents under pressure. Do not puncture or incinerate. Do not store at temperature above 120ºF
- do not bandage tightly
- do not use with a heating pad, medicated patch or other types of local heat
- do not apply to wounds or damaged, broken or irritated skin

Stop use and ask a doctor if

- condition worsens or irritation develops
- pain, swelling or blistering develops where product was applied
- redness or severe burning develops where product was applied
- symptoms persist for more than 7 days or clear up and occur again within a few days

PREGNANCY OR BREAST FEEDING

If pregnant or breast-feeding, ask a health professional before use.

KEEP OUT OF REACH OF CHILDREN

If swallowed, get medical help or contact a Poison Control Center right away.

Directions

Adults and children 12 years of age and older | - Shake well before use - Apply to affected area not more than 3 to 4 times daily - Do not apply to face - Use in a well-ventilated area and avoid inhalation - Wash hands with soap and water after use if product comes in contact with hands
Children under 12 years of age | - Ask a doctor

Other information

- store between 20º-25ºC (68º-77ºF)

Inactive ingredients

boswellia carterii oil, clove oil, dimethylaminoethyl methacrylate copolymer, dimethyl isosorbide, eucalyptus oil, fragrance, isobutane, isopentane, isopulegol, linseed oil, menthoxypropanediol, pepermint oil, propane, propanediol, rosemary oil, SD alcohol 40-B (13% v/v), thymus mastichina flower oil, tocopherol, vanillyl butyl ether, vinyl caprolactam, vinylpyrrolidone

Questions

1-800-395-0689

Package label display

ALEVEX™

PAIN RELIEVING

SPRAY

MAX

STRENGTH

MENTHOL

COOLS IN

SECONDS

FOR EXTERNAL

USE ONLY

NET WT 3.2 OZ (91 g)